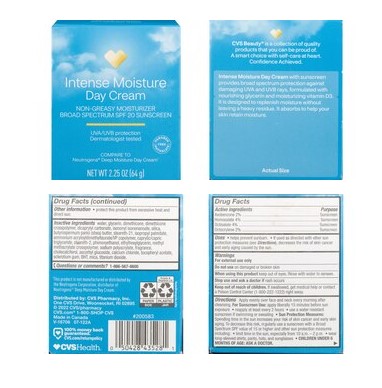 DRUG LABEL: Intense Moisture Day Cream
NDC: 51316-528 | Form: LOTION
Manufacturer: CVS Health
Category: otc | Type: HUMAN OTC DRUG LABEL
Date: 20260119

ACTIVE INGREDIENTS: AVOBENZONE 20 mg/1 g; HOMOSALATE 40 mg/1 g; OCTISALATE 40 mg/1 g; OCTOCRYLENE 20 mg/1 g
INACTIVE INGREDIENTS: WATER; GLYCERIN; DIMETHICONE; DIMETHICONE CROSSPOLYMER; DICAPRYLYL CARBONATE; ISONONYL ISONONANOATE; SILICA; BUTYROSPERMUM PARKII (SHEA) BUTTER; STEARETH-21; ISOPROPYL PALMITATE; AMMONIUM ACRYLOYL DIMETHYLTAURATE/METHACRYLATE, DIMETHYLACRYLAMIDE AND METHACRYLIC ACID COPOLYMER, PPG-3 GLYCERYL TRIACRYLATE CROSSLINKED (100000 MW); CAPRYLIC/CAPRIC TRIGLYCERIDE; STEARETH-2; PHENOXYETHANOL; ETHYLHEXYLGLYCERIN; METHYL METHACRYLATE; SODIUM POLYACRYLATE (2500000 MW); FRAGRANCE 13576; CHOLECALCIFEROL; ASCORBYL GLUCOSIDE; CALCIUM CHLORIDE; .ALPHA.-TOCOPHEROL ACETATE; SCLEROTIUM GUM; BHT; MICA; TITANIUM DIOXIDE

Tiege Hanley AM Morning Facial Moisturizer with SPF 20
0.75 FL OZ (22ml) & 2.5 FL OZ (75 ml)

Active Ingredient

Active Ingredients
Avobenzene 2%

Homosalate 4%

Octisalate 4%

Octocrylene 2.0%

Purpose

SUNSCREEN

Uses

- Helps prevent sunburn

- If used as directed with other sun protection measures (see Directions), decreases the risk of skin cancer and early aging caused by the sun.

Warnings

■ For external use only
■ Do not use on damaged or broken skin

■ When using this product, keep out of eyes. Rinse with water to remove
■ Stop use and ask a doctor if rash occurs

Keep out of reach of children.

■ If swallowed, get medical help or contact a Poison Control Center (1-800-222-1222) right away

Directions

Apply evenly over face and neck every morning after cleansing. For Sunscreen Use: apply liberally 15 minutes before sun exposure-reapply at least every 2 hours- use a water resistant sunscreen if swimming or sweating. Sun Protection Measures: Spending time in the sun increases your risk of skin cancer an early skin aging. To decrease this risk, regularly use a sunscreen with a Broad Spectrum SPF value of 15 or higher and other sun protection measures including: limit time in the sun especially from 10am to 2pm, wear long sleeved shirts, pants, hats and sunglasses, children under 6 months age: Ask a doctor.

Inactive Ingredients

Water, Glycerin, Dimethicone, Dimethicone Crosspolymer, Dicaprylyl Carbonate, Isopropyl Isononanoate, Silica, Butyrospermum Parkii (Shea) Butter, Steareth -21, Isopropyl Palmitate, Ammonium Acryloyldimethyltaurate/VP Copolymer, Caprylic/Capric Triglyceride, Steareth-2, Phenoxyethanol, Ethylhexylglycerin, Methyl Methacrylate Crosspolymer, Sodium Polyacrylate, Fragrance, Cholecalciferol, Ascorbyl Glucoside, Calcium Chloride, Tocopheryl Acetate, Sclerotium Gum, BHT, Mica, Titanium Dioxide

PDP

Intense Moisture

Day Cream

NON-GREASY MOISTURIZER

BROAD SPECTRUM SPF 20 SUNSCREEN

UVA/UVB protection

Dermatologist tested

COMPARE TO Neutrogena Deep Moisture Day Cream

NET WT 2.25 OZ (64 g)

Intense Moisture Day Cream